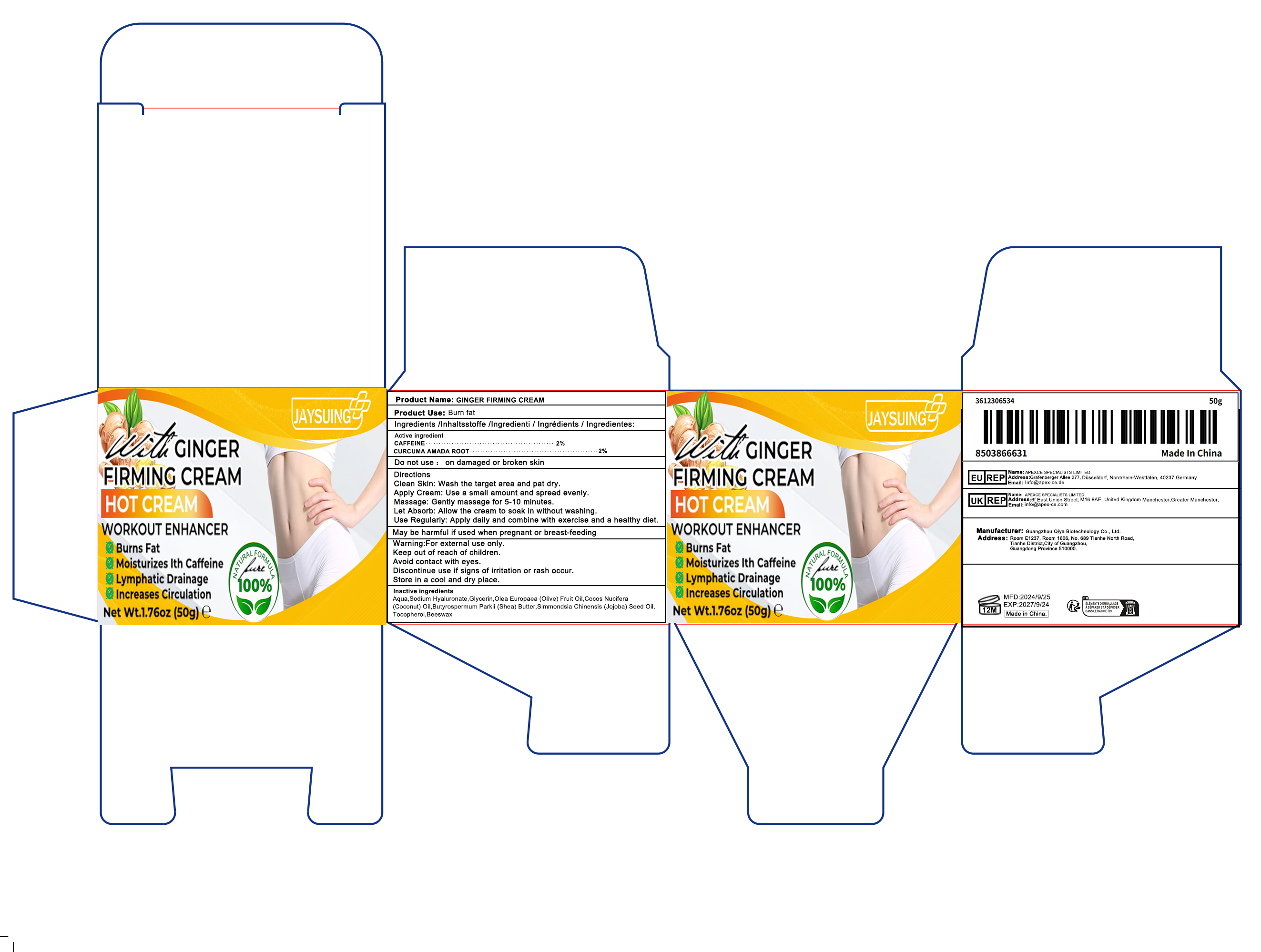 DRUG LABEL: Jaysuing Thermal Body Massage Cream with Turmeric Shea Coconut Oil
NDC: 84793-005 | Form: CREAM
Manufacturer: Guangzhou Qiya Biotechnology Co., Ltd
Category: otc | Type: HUMAN OTC DRUG LABEL
Date: 20241105

ACTIVE INGREDIENTS: CAFFEINE 2 g/2 g; CURCUMA AMADA ROOT 2 g/2 g
INACTIVE INGREDIENTS: WATER 2 g/2 g; SODIUM HYALURONATE 2 g/2 g

Purpose

Burn fat

Uses

Helps burn fat

Clean Skin: Wash the target area and pat dry.
Apply Cream: Use a small amount and spread evenly.
Massage: Gently massage for 5-10 minutes.
Let Absorb: Allow the cream to soak in without washing.
Use Regularly: Apply daily and combine with exercise and a healthy diet.

Warnings

For external use only

Stop use and ask a doctor if

rash occurs

Do not use

on damaged or broken skin

Keep out of reach of children.

If swallowed, qet medical help or contact a Poison Control Center right away.

When using this product

keep out of eyes. Rinse with water to remove.

Dosage and Management

Recommended Amount: Approximately 5 grams per application.
Frequency of Use: Apply twice daily, morning and night.
Application Method: Clean the target area, apply evenly, and massage gently for 2-5 minutes.

inactive ingredients

Butyrospermum Parkii (Shea) Butter 9%
Cocos Nucifera (Coconut) Oil 9%
Glycerin 10%
Sodium Hyaluronate 10%
Simmondsia Chinensis (Jojoba) Seed Oil 10%
Olea Europaea (Olive) Fruit Oil 10%
Aqua 16%
Tocopherol 8%
Beeswax 8%